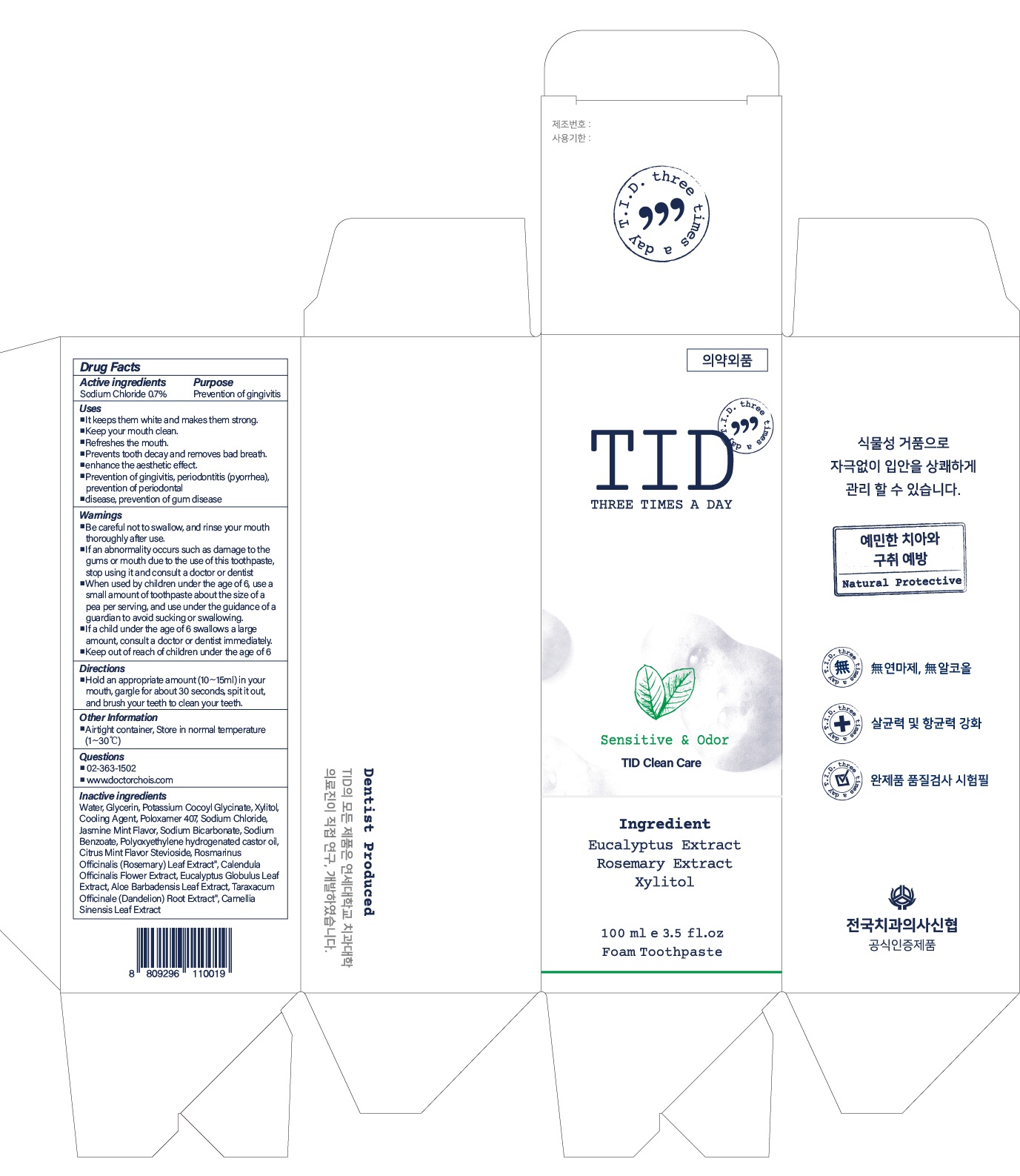 DRUG LABEL: TID Clean Care
NDC: 73666-0560 | Form: PASTE, DENTIFRICE
Manufacturer: Doctor Choi`s Korea Co., LTD.
Category: otc | Type: HUMAN OTC DRUG LABEL
Date: 20221007

ACTIVE INGREDIENTS: Sodium Chloride 0.7 g/100 mL
INACTIVE INGREDIENTS: Water; Glycerin; Potassium Cocoyl Glycinate

ACTIVE INGREDIENTS

Sodium Chloride 0.7%

PURPOSE

Prevention of gingivitis

Uses

■ It keeps them white and makes them strong.
■ Keep your mouth clean.
■ Refreshes the mouth.
■ Prevents tooth decay and removes bad breath.
■ enhance the aesthetic effect.
■ Prevention of gingivitis, periodontitis (pyorrhea), prevention of periodontal
■ disease, prevention of gum disease

WARNINGS

■ Be careful not to swallow, and rinse your mouth thoroughly after use.
■ If an abnormality occurs such as damage to the gums or mouth due to the use of this toothpaste, stop using it and consult a doctor or dentist
■When used by children under the age of 6, use a small amount of toothpaste about the size of a pea per serving, and use under the guidance of a guardian to avoid sucking or swallowing.
■If a child under the age of 6 swallows a large amount, consult a doctor or dentist immediately.
■Keep out of reach of children under the age of 6

■Keep out of reach of children under the age of 6

Directions

■Hold an appropriate amount (10~15ml) in your mouth, gargle for about 30 seconds, spit it out, and brush your teeth to clean your teeth.

Other Information

■ Airtight container, Store in normal temperature (1~30℃)

Questions

■ 02-363-1502
■ www.doctorchois.com

INACTIVE INGREDIENTS

Water, Glycerin, Potassium Cocoyl Glycinate, Xylitol, Cooling Agent, Poloxamer 407, Sodium Chloride, Jasmine Mint Flavor, Sodium Bicarbonate, Sodium Benzoate, Polyoxyethylene hydrogenated castor oil, Citrus Mint Flavor, Stevioside, Rosmarinus Officinalis (Rosemary) Leaf Extract", Calendula Officinalis Flower Extract, Eucalyptus Globulus Leaf Extract, Aloe Barbadensis Leaf Extract, Taraxacum Officinale (Dandelion) Root Extract", Camellia Sinensis Leaf Extract